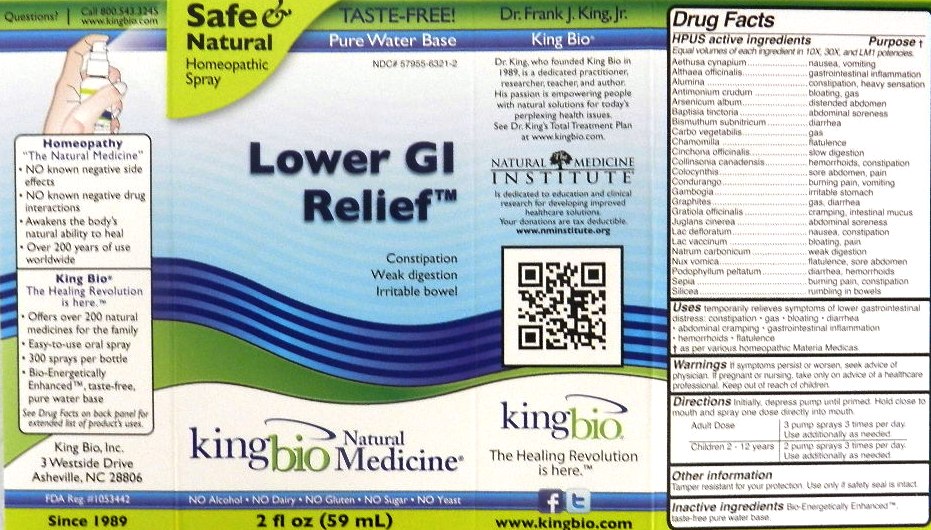 DRUG LABEL: Lower GI Relief
NDC: 57955-6321 | Form: LIQUID
Manufacturer: King Bio Inc.
Category: homeopathic | Type: HUMAN OTC DRUG LABEL
Date: 20111117

ACTIVE INGREDIENTS: AETHUSA CYNAPIUM 10 [hp_X]/59 mL; ALTHAEA OFFICINALIS ROOT 10 [hp_X]/59 mL; ALUMINUM OXIDE 10 [hp_X]/59 mL; ANTIMONY TRISULFIDE 10 [hp_X]/59 mL; ARSENIC TRIOXIDE 10 [hp_X]/59 mL; BAPTISIA TINCTORIA ROOT 10 [hp_X]/59 mL; BISMUTH SUBNITRATE 10 [hp_X]/59 mL; ACTIVATED CHARCOAL 10 [hp_X]/59 mL; MATRICARIA RECUTITA 10 [hp_X]/59 mL; CINCHONA OFFICINALIS BARK 10 [hp_X]/59 mL; COLLINSONIA CANADENSIS ROOT 10 [hp_X]/59 mL; CITRULLUS COLOCYNTHIS FRUIT PULP 10 mL/59 mL; GAMBOGE 10 [hp_X]/59 mL; GRAPHITE 10 [hp_X]/59 mL; GRATIOLA OFFICINALIS 10 [hp_X]/59 mL; JUGLANS CINEREA BRANCH BARK/ROOT BARK 10 [hp_X]/59 mL; SKIM MILK 10 [hp_X]/59 mL; COW MILK 10 [hp_X]/59 mL; SODIUM CARBONATE 10 [hp_X]/59 mL; STRYCHNOS NUX-VOMICA SEED 10 [hp_X]/59 mL; PODOPHYLLUM 10 [hp_X]/59 mL; SEPIA OFFICINALIS JUICE 10 [hp_X]/59 mL; SILICON DIOXIDE 10 [hp_X]/59 mL
INACTIVE INGREDIENTS: WATER

Lower GI Relief

Active Ingredients

HPUS active ingredients

Equal volumes of each ingredient in 10X, 30X, and LM1 potencies.

Aethusa cynapium

Althaea officinalis

Alumina

Antimonium crudum

Arsenicum album

Baptisia tinctoria

Bismuthum subnitricum

Carbo vegetabilis

Chamomilla

Cinchona officinalis

Collinsonia canadensis

Colocynthis

Condurango

Gambogia

Graphites

Gratiola officinalis

Juglans cinerea

Lac defloratum

Lac vaccinum

Natrum carbonicum

Nux vomica

Podophyllum peltatum

sepia

Silicea

Reference image lower gi.jpg

Inactive Ingredient

Bio-Energetically Enhanced, taste-free pure water base.

Reference image lower gi.jpg

Purpose

HPUS active ingredients Purpose

Equal volumes of each ingredient in 10X, 30X, and LM1 potencies.

Aethusa cynapium.........................................nausea, vomiting

Althaea officinalis...........................................gastrointestinal inflammation

Alumina.........................................................constipation, heavy sensation

Antimonium crudum.......................................bloating, gas

Arsenicum album...........................................distended abdomen

Baptisia tinctoria............................................abdominal soreness

Bismuthum subnitricum..................................diarrhea

Carbo vegetabilis...........................................gas

Chamomilla...................................................flatulence

Cinchona officinalis........................................slow digestion

Collinsonia canadensis...................................hemorrhoids, constipation

Colocynthis...................................................sore abdomen, pain

Condurango..................................................burning pain, vomiting

Gambogia.....................................................irritable stomach

Graphites.....................................................gas, diarrhea

Gratiola officinalis.........................................cramping, intestinal mucus

Juglans cinerea............................................abdominal soreness

Lac defloratum.............................................nausea, constipation

Lac vaccinum..............................................bloating, pain

Natrum carbonicum......................................weak digestion

Nux vomica.................................................flatulence, sore abdomen

Podophyllum peltatum..................................diarrhea, hemorrhoids

Sepia...........................................................burning pain, constipation

Silicea..........................................................rumbling in bowels

Reference image lower gi.jpg

Warnings

If symptoms persist or worsen, seek advice of physician. If pregnant or nursing, take only on advice of a healthcare professional. Keep out of reach of children.

Other information

Tamper resistant for your protection. Use only if safety seal is intact.

Reference image lower gi.jpg

Keep out of reach of children

Reference image lower gi.jpg

Dosage

Directions Initially, depress pump until primed. Hold close to mouth and spray one dose directly into mouth.

Adult Dose- 3 pump sprays 3 times per day. Use additionally as needed.

Children 2-12 years- 2 pump sprays 3 times per day. Use additionally as needed.

Reference image lower gi.jpg

Indications and Usage

Uses temporarily relieves symptoms of lower gastrointestinal distress:

- constipation
- gas
- bloating
- diarrhea
- abdominal cramping
- gastrointestinal inflammation
- hemorrhoids
- flatulence

as per various homeopathic Materia Medicas.
Reference image lower gi.jpg

PACKAGE LABEL

King Bio Inc.

3 Westside Drive

Asheville, NC 28806

www.kingbio.com

Reference image lower gi.jpg